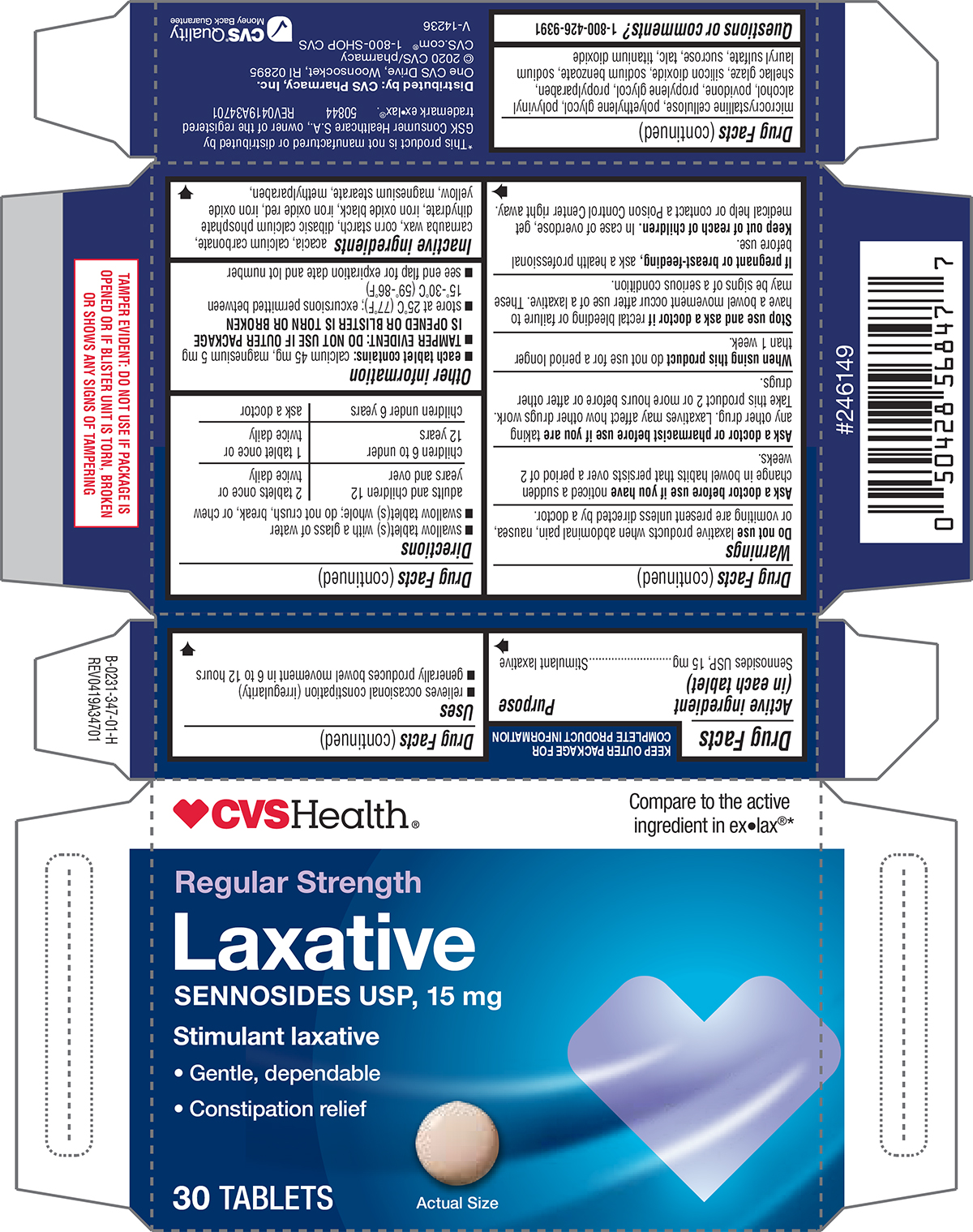 DRUG LABEL: Laxative
NDC: 69842-347 | Form: TABLET, SUGAR COATED
Manufacturer: CVS PHARMACY
Category: otc | Type: HUMAN OTC DRUG LABEL
Date: 20250607

ACTIVE INGREDIENTS: SENNOSIDES 15 mg/1 1
INACTIVE INGREDIENTS: ACACIA; CALCIUM CARBONATE; CARNAUBA WAX; STARCH, CORN; DIBASIC CALCIUM PHOSPHATE DIHYDRATE; FERROSOFERRIC OXIDE; FERRIC OXIDE RED; FERRIC OXIDE YELLOW; MAGNESIUM STEARATE; METHYLPARABEN; MICROCRYSTALLINE CELLULOSE; POLYETHYLENE GLYCOL, UNSPECIFIED; POLYVINYL ALCOHOL, UNSPECIFIED; POVIDONE, UNSPECIFIED; PROPYLENE GLYCOL; PROPYLPARABEN; SHELLAC; SILICON DIOXIDE; SODIUM BENZOATE; SODIUM LAURYL SULFATE; SUCROSE; TALC; TITANIUM DIOXIDE

CVS 44-347

Active ingredient (in each tablet)

Sennosides USP, 15 mg

Purpose

Stimulant laxative

Uses

- relieves occasional constipation (irregularity)
- generally produces bowel movement in 6 to 12 hours

Warnings

Do not use

laxative products when abdominal pain, nausea, or vomiting are present unless directed by a doctor.

Ask a doctor before use if you have

noticed a sudden change in bowel habits that persists over a period of 2 weeks.

Ask a doctor or pharmacist before use if you are

taking any other drug. Laxatives may affect how other drugs work. Take this product 2 or more hours before or after other drugs.

When using this product

do not use for a period longer than 1 week.

Stop use and ask a doctor if

rectal bleeding or failure to have a bowel movement occur after use of a laxative. These may be signs of a serious condition.

If pregnant or breast-feeding,

ask a health professional before use.

Keep out of reach of children.

In case of overdose, get medical help or contact a Poison Control Center right away.

Directions

- swallow tablet(s) with a glass of water
- swallow tablet(s) whole; do not crush, break, or chew

adults and children 12 years and over | 2 tablets once or twice daily
children 6 to under 12 years | 1 tablet once or twice daily
children under 6 years | ask a doctor

Other information

- each tablet contains: calcium 45 mg, magnesium 5 mg
- TAMPER EVIDENT: DO NOT USE IF OUTER PACKAGE IS OPENED OR BLISTER IS TORN OR BROKEN
- store at 25°C (77°F); excursions permitted between 15°-30°C (59°-86°F)
- see end flap for expiration date and lot number

Inactive ingredients

acacia, calcium carbonate, carnauba wax, corn starch, dibasic calcium phosphate dihydrate, iron oxide black, iron oxide red, iron oxide yellow, magnesium stearate, methylparaben, microcrystalline cellulose, polyethylene glycol, polyvinyl alcohol, povidone, propylene glycol, propylparaben, shellac glaze, silicon dioxide, sodium benzoate, sodium lauryl sulfate, sucrose, talc, titanium dioxide

Questions or comments?

1-800-426-9391

Principal display panel

CVSHealth®

Compare to the active
ingredient in ex•lax®*

Regular Strength
Laxative
SENNOSIDES USP, 15 mg

Stimulant laxative

• Gentle, dependable
• Constipation relief

30 TABLETS

Actual Size

TAMPER EVIDENT: DO NOT USE IF PACKAGE IS
OPENED OR IF BLISTER UNIT IS TORN, BROKEN
OR SHOWS ANY SIGNS OF TAMPERING

*This product is not manufactured or distributed by
GSK Consumer Healthcare S.A., owner of the registered
trademark ex•lax®. 50844 REV0419A34701

Distributed by: CVS Pharmacy, Inc.
One CVS Drive, Woonsocket, RI 02895
© 2020 CVS/pharmacy
CVS.com® 1-800-SHOP CVS

V-14236

CVS®Quality
Money Back Guarantee

CVS 44-347